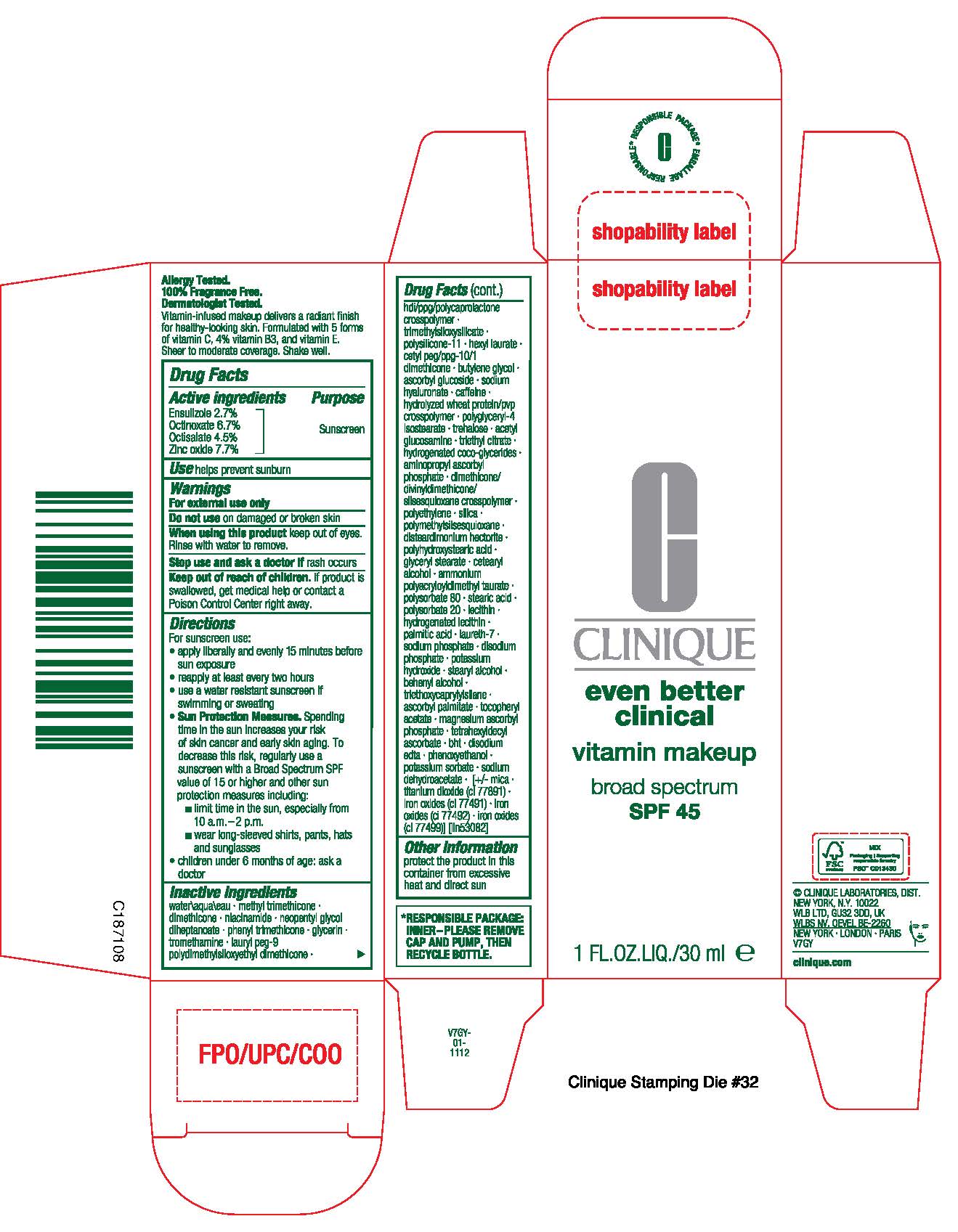 DRUG LABEL: EVEN BETTER CLINICAL VITAMIN MAKEUP BROAD SPECTRUM SPF 45
NDC: 49527-220 | Form: LIQUID
Manufacturer: CLINIQUE LABORATORIES LLC
Category: otc | Type: HUMAN OTC DRUG LABEL
Date: 20251230

ACTIVE INGREDIENTS: ZINC OXIDE 77 mg/1 mL; ENSULIZOLE 27 mg/1 mL; OCTINOXATE 67 mg/1 mL; OCTISALATE 45 mg/1 mL
INACTIVE INGREDIENTS: POLYGLYCERYL-4 ISOSTEARATE; TRIETHYL CITRATE; CETOSTEARYL ALCOHOL; POTASSIUM SORBATE; SODIUM DEHYDROACETATE; PHENYL TRIMETHICONE; HYALURONATE SODIUM; DIMETHICONE/DIVINYLDIMETHICONE/SILSESQUIOXANE CROSSPOLYMER; SILICON DIOXIDE; STEARYL ALCOHOL; DOCOSANOL; DIMETHICONE; LAURETH-7; LAURYL PEG-9 POLYDIMETHYLSILOXYETHYL DIMETHICONE; HEXYL LAURATE; STEARIC ACID; SODIUM PHOSPHATE; ASCORBYL PALMITATE; TITANIUM DIOXIDE; FERROSOFERRIC OXIDE; FERRIC OXIDE RED; WATER; BUTYLATED HYDROXYTOLUENE; MAGNESIUM ASCORBYL PHOSPHATE; EDETATE DISODIUM ANHYDROUS; NEOPENTYL GLYCOL DIHEPTANOATE; TREHALOSE; HYDROGENATED SOYBEAN LECITHIN; .ALPHA.-TOCOPHEROL ACETATE; ASCORBYL GLUCOSIDE; POLYSORBATE 20; CAFFEINE; DISTEARDIMONIUM HECTORITE; AMMONIUM POLYACRYLOYLDIMETHYL TAURATE; PHENOXYETHANOL; DIMETHICONE/VINYL DIMETHICONE CROSSPOLYMER (SOFT PARTICLE); HIGH DENSITY POLYETHYLENE; POTASSIUM HYDROXIDE; SOYBEAN; TRIETHOXYCAPRYLYLSILANE; CETYL PEG/PPG-10/1 DIMETHICONE (HLB 5); POLYHYDROXYSTEARIC ACID (2300 MW); PALMITIC ACID; SODIUM PHOSPHATE, DIBASIC, ANHYDROUS; N-ACETYLGLUCOSAMINE; TROMETHAMINE; TRIMETHYLSILOXYSILICATE (M/Q 0.6-0.8); MICA; GLYCERYL MONOSTEARATE; METHYL TRIMETHICONE; NIACINAMIDE; HYDROGENATED COCO-GLYCERIDES; AMINOPROPYL ASCORBYL PHOSPHATE; FERRIC OXIDE YELLOW; POLYSORBATE 80; GLYCERIN; BUTYLENE GLYCOL; POLYMETHYLSILSESQUIOXANE (4.5 MICRONS); TETRAHEXYLDECYL ASCORBATE

EVEN BETTER CLINICAL VITAMIN MAKEUP BROAD SPECTRUM SPF 45

Active ingredients

ENSULIZOLE 2.7%
OCTINOXATE 6.7%
OCTISALATE 4.5%
ZINC OXIDE 7.7%

Purpose

Sunscreen

Use

helps prevent sunburn

For external use only

Do not use

on damaged or broken skin

When using this product

keep out of eyes. Rinse with water to remove.

Stop use

and ask a doctor if rash occurs

Keep out of reach of children.

If product is swallowed, get medical help or contact a Poison Control Center right away.

Directions

For sunscreen use:
apply liberally 15 minutes before sun exposure
reapply at least every two hours
use a water resistant sunscreen if swimming or sweating
Sun Protection Measures. Spending time in the sun increases your risk of skin cancer and early skin aging. To decrease this risk, regularly use a sunscreen with a Broad Spectrum SPF value of 15 or higher and other sun protection measures including:
limit time in the sun, especially from 10 a.m.–2 p.m.
wear long-sleeved shirts, pants, hats and sunglasses
children under 6 months of age: ask a doctor

Inactive ingredients

water\aqua\eau,methyl trimethicone,dimethicone,niacinamide,neopentyl glycol diheptanoate,phenyl trimethicone,glycerin,tromethamine,lauryl peg-9 polydimethylsiloxyethyl dimethicone,hdi/ppg/polycaprolactone crosspolymer,trimethylsiloxysilicate,polysilicone-11,hexyl laurate,cetyl peg/ppg-10/1 dimethicone,butylene glycol,ascorbyl glucoside,sodium hyaluronate,caffeine,hydrolyzed wheat protein/pvp crosspolymer,polyglyceryl-4 isostearate,trehalose,acetyl glucosamine,triethyl citrate,hydrogenated coco-glycerides,aminopropyl ascorbyl phosphate,dimethicone/divinyldimethicone/silsesquioxane crosspolymer,polyethylene,silica,polymethylsilsesquioxane,disteardimonium hectorite,polyhydroxystearic acid,glyceryl stearate,cetearyl alcohol,ammonium polyacryloyldimethyl taurate,polysorbate 80,stearic acid,polysorbate 20,lecithin,hydrogenated lecithin,palmitic acid,laureth-7,sodium phosphate,disodium phosphate,potassium hydroxide,stearyl alcohol,behenyl alcohol,triethoxycaprylylsilane,ascorbyl palmitate,tocopheryl acetate,magnesium ascorbyl phosphate,tetrahexyldecyl ascorbate,bht,disodium edta,phenoxyethanol,potassium sorbate,sodium dehydroacetate, [+/- mica,titanium dioxide (ci 77891),iron oxides (ci 77491),iron oxides (ci 77492),iron oxides (ci 77499)] <iln53082>

Other information

protect the product in this container from excessive heat and direct sun

PACKAGE LABEL

CLINIQUE

even better clinical

vitamon makeup

broad spectrum SPF 45

1 FL.OZ.LIQ/30 ml